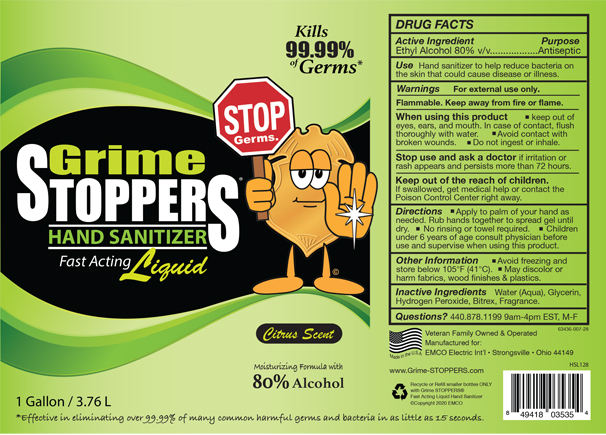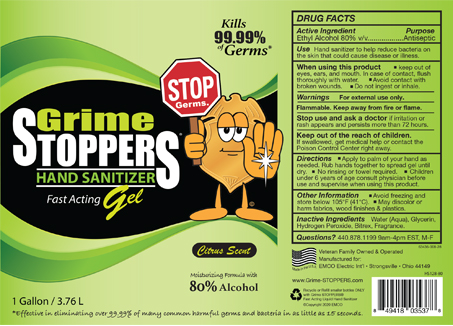 DRUG LABEL: Grime STOPPERS Fast Acting Hand Sanitizer Liquid
NDC: 63436-007 | Form: LIQUID
Manufacturer: EMCO Electric International
Category: otc | Type: HUMAN OTC DRUG LABEL
Date: 20200828

ACTIVE INGREDIENTS: ALCOHOL 80 mL/100 mL
INACTIVE INGREDIENTS: GLYCERIN 1.5 mL/100 mL; DENATONIUM BENZOATE 0.01 mL/100 mL; HYDROGEN PEROXIDE 0.2 mL/100 mL; WATER 18 mL/100 mL

Hand Sanitizer

ACTIVE INGREDIENT

Ethyl Alcohol 80% v/v

PURPOSE

Antiseptic

USE

Hand Sanitzer to help reduce bacteria on the skin that could cause disease or illness.

DOSAGE AND ADMINISTRATION

Topical Liquid applied to outer surface of the body, specifcially hands.

WARNINGS

- For external use only.
- Flammable. Keep away from fire or flame.

When using this product

- keep out of eyes, ears, and mouth. In case of contact, flush thoroughly with water.
- Avoid contact with open wounds.
- Do not ingest or inhale.

Stop us and ask a doctor

if irritation or rash appears and persists more than 72 hours.

Keep out of the reach of children.

If swallowed, get medical help or contact the Poison Control Center right away.

DIRECTIONS

- Apply to palm of your hands as needed. Rub hands together to spread gel until dry.
- No rinsing or towel required.
- Children under 6 years of age consult physician before use and supervise when using this product.

OTHER INFORMATION

- Avoid freezing and store below 105°F (41°C).
- May discolor or harm fabrics, wood finishes & plastics.

INACTIVE INGREDIENTS

- Water
- Glycerin
- Hydrogen Peroxide
- Biterex
- Fragrance

Label

Liquid Application 1 Gallon (3.76L) NDC: 43636-007-28

Label

Gel Application 1 Gallon (3.76L) NDC: 43636-008-28